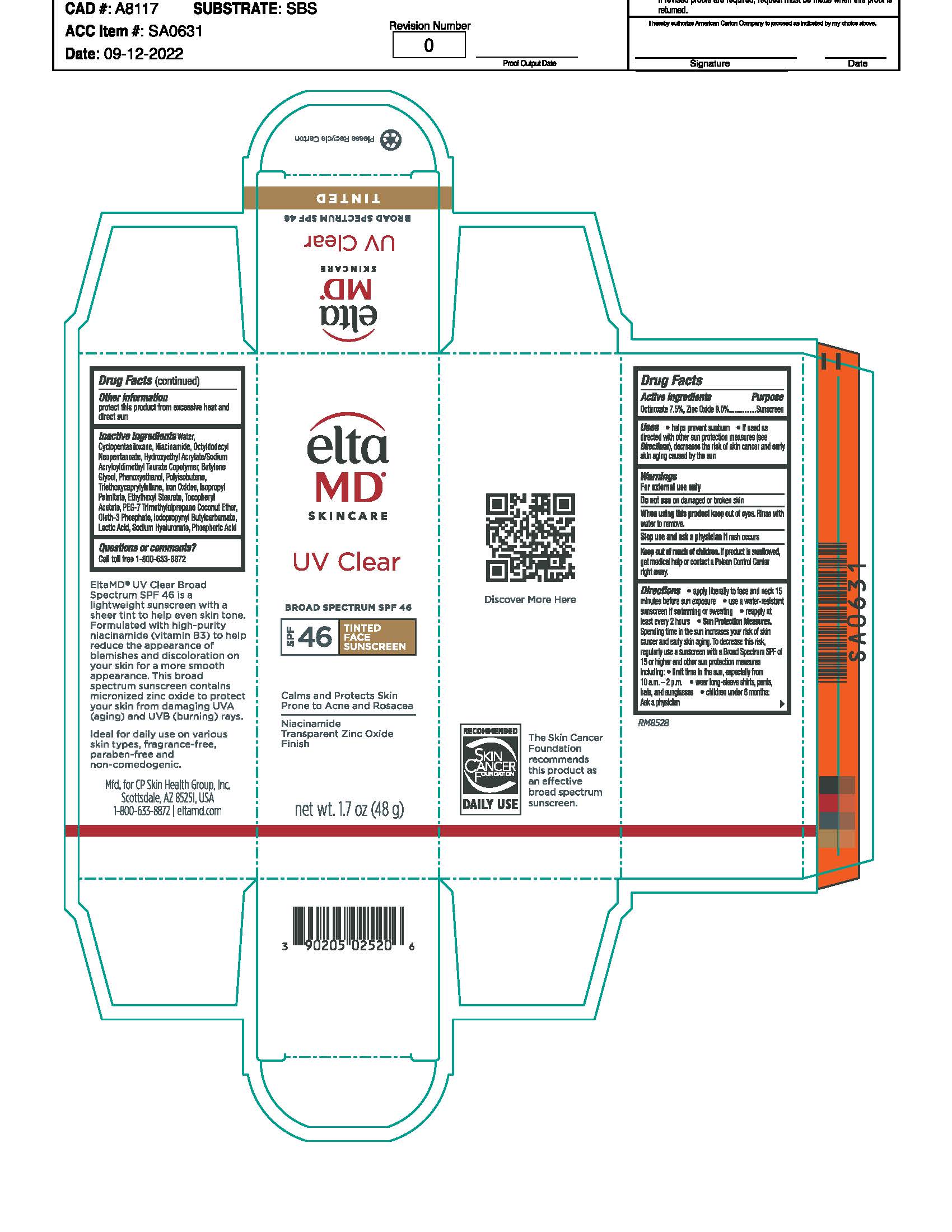 DRUG LABEL: EltaMD UV Clear Tinted SPF46
NDC: 72043-2520 | Form: LOTION
Manufacturer: CP Skin Health Group, Inc.
Category: otc | Type: HUMAN OTC DRUG LABEL
Date: 20250331

ACTIVE INGREDIENTS: ZINC OXIDE 90 g/1000 g; OCTINOXATE 75 g/1000 g
INACTIVE INGREDIENTS: BUTYLENE GLYCOL; PHENOXYETHANOL; WATER; LACTIC ACID; HYALURONATE SODIUM; NIACINAMIDE; ISOPROPYL PALMITATE; OCTYL STEARATE; OCTYLDODECYL NEOPENTANOATE; OLETH-3 PHOSPHATE; CYCLOMETHICONE 5; .ALPHA.-TOCOPHEROL ACETATE, DL-; TRIETHOXYCAPRYLYLSILANE; HYDROXYETHYL ACRYLATE/SODIUM ACRYLOYLDIMETHYL TAURATE COPOLYMER (100000 MPA.S AT 1.5%); POLYISOBUTYLENE (1000 MW); FERRIC OXIDE YELLOW; FERRIC OXIDE RED; FERROSOFERRIC OXIDE

EltaMD UV Clear Tinted SPF46

Warnings

For external use only. Do not use on damaged or broken skin. When using the product keep out of eyes. Rinse with water to remove Stop use and ask a physician if rash occurs. If product is swallowed, get medical help or contact a Poison Control Center right away. Keep out of reach of children.

Active Ingredients

Zinc Oxide 9.0% Sunscreen

Octinoxate 7.5% Sunscreen

Uses

helps prevent sunburn. if used as directed with other sun protection measures (see directions), decreases the risk of skin cancer and early skin aging caused by the sun

Uses

helps prevent sunburn. if used as directed with other sun protection measures (see directions), decreases the risk of skin cancer and early skin aging caused by the sun

Directions

apply liberally to face and neck 15 minutes before sun exposure. use a water resistant sunscreen if swimming or sweating. reapply at least every 2 hours. Sun Protection Measures: Spending time in the sun increases your risk of skin cancer and early skin aging. To decrease this risk, regularly use a sunscreen with a broad spectrum SPF of 15 or higher and other sun protection measures including: limit time in the sun, especially from 10 a.m. - 2 p.m., wear long-sleeve shirts, pants, hats and sunglasses. children under 6 months: ask a physician

Inactive Ingredients

purified water, cyclopentasiloxane, nicacinamide, octyldodecyl neopentanoate, butylene glycol, hydroxyethyl acrylate/sodium acryloyldimethyl taurate copolymer, polyisobutene, PEG-7 trimethylolpropane coconut ether, sodium hyaluronate, tocopheryl acetate, lactic acid, oleth-3 phosphate, phenoxyethanol, iodopropynyl butylcarbamate, isopropyl palmitate, octyl stearate, iron oxides, triethoxycaprylylsilane

KEEP OUT OF REACH OF CHILDREN